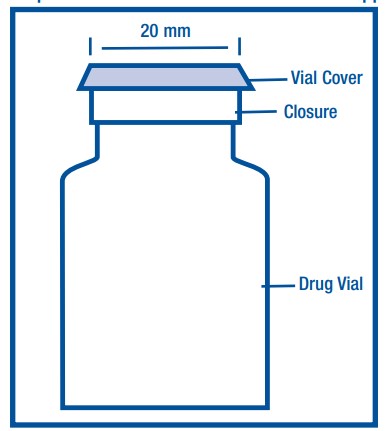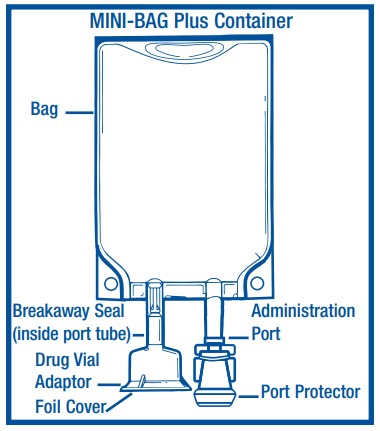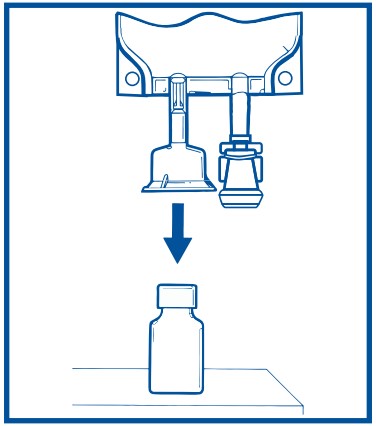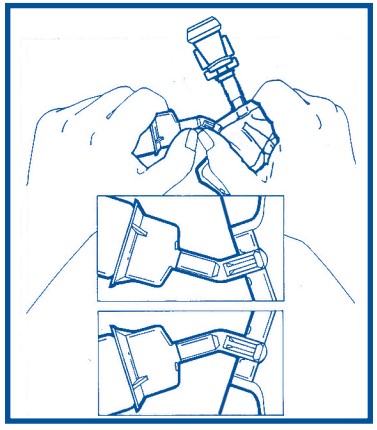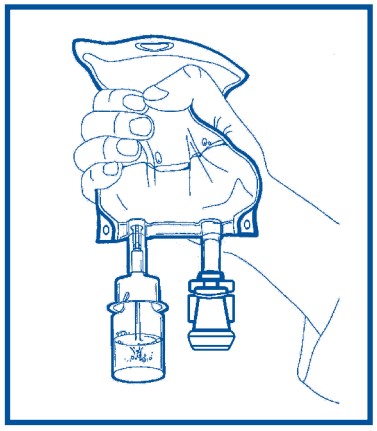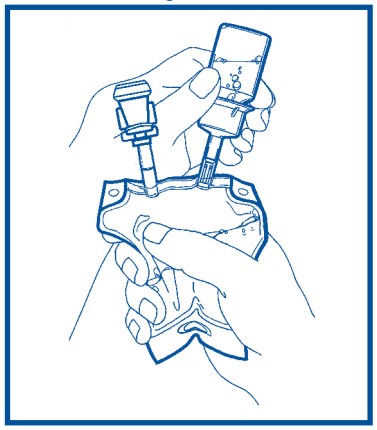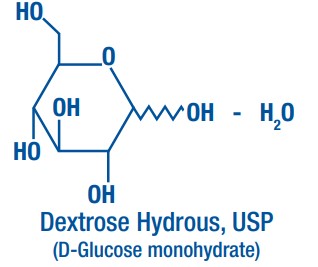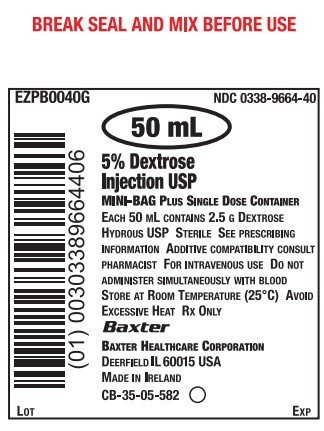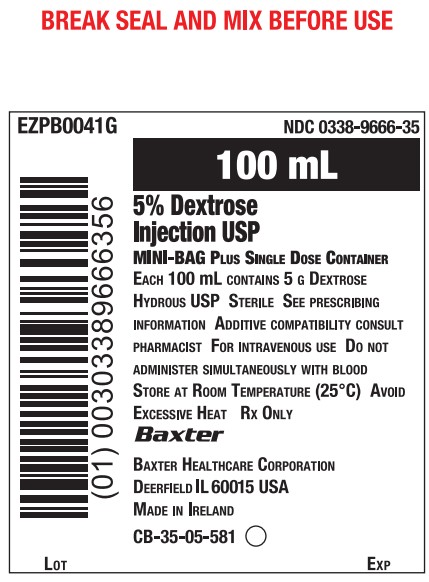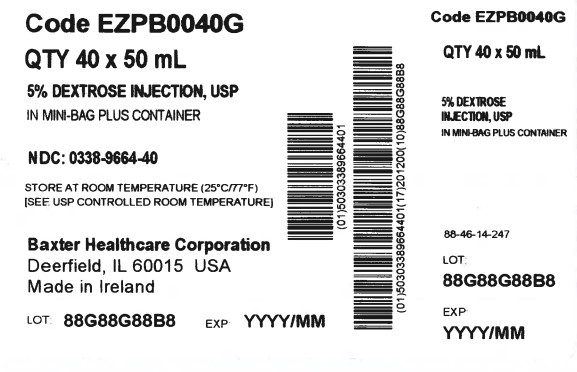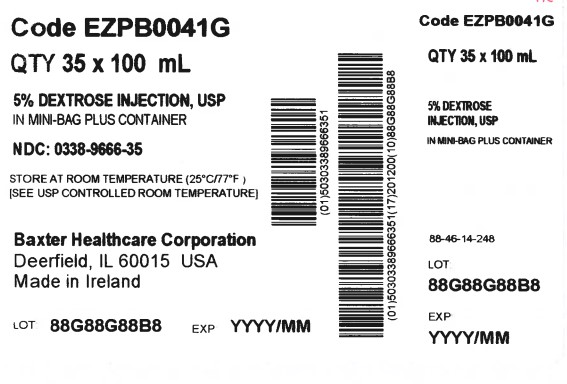 DRUG LABEL: Dextrose
NDC: 0338-9664 | Form: INJECTION
Manufacturer: Baxter Healthcare Company
Category: prescription | Type: HUMAN PRESCRIPTION DRUG LABEL
Date: 20250730

ACTIVE INGREDIENTS: DEXTROSE MONOHYDRATE 2.5 g/50 mL
INACTIVE INGREDIENTS: WATER

HIGHLIGHTS OF PRESCRIBING INFORMATION

These highlights do not include all the information needed to use DEXTROSE INJECTION safely and effectively. See full prescribing information for DEXTROSE INJECTION.
DEXTROSE Injection, for intravenous use
Initial U.S. Approval: 1940

1 INDICATIONS AND USAGE

Dextrose Injection is indicated as a source of calories and water and may also be used as diluent for reconstitution of a powdered or liquid (up to 10 mL) drug product packaged in a vial with a 20 mm closure. (1)

2 DOSAGE AND ADMINISTRATION

- Only for intravenous infusion. (2.1)
- See full prescribing information for information on preparation, administration, dosing considerations and instructions for use. (2.1, 2.2, 2.3)

3 DOSAGE FORMS AND STRENGTHS

Injection: 5% (0.05 grams/mL), 5 grams of dextrose hydrous per 100 mL in 50 mL and 100 mL single-dose, flexible containers (3)

4 CONTRAINDICATIONS

- Clinically significant hyperglycemia. (4)
- Known hypersensitivity to dextrose. (4)

5 WARNINGS AND PRECAUTIONS

- Hyperglycemia or Hyperosmolar Hyperglycemic State: Monitor blood glucose and administer insulin as needed. (5.1)
- Hypersensitivity Reactions : Monitor for signs and symptoms and discontinue infusion if reactions occur. (5.2)
- Vein Damage and Thrombosis: Consider central vein when administering more than 5% dextrose or with an osmolarity of ≥ 900 mOsm/L or when there is peripheral vein irritation, phlebitis, and/or associated pain. (2.2, 5.3)
- Hyponatremia: Avoid in patients with or at risk for hyponatremia. If use cannot be avoided, monitor serum sodium concentrations (5.4)
- Electrolyte Imbalance and Fluid Overload: Avoid in patients with or at risk for fluid and/or solute overloading. If use cannot be avoided, monitor daily fluid balance, electrolyte concentrations, and acid-base balance, as needed and especially during prolonged use (5.5)
- Refeeding Syndrome: Monitor severely undernourished patients and slowly increase nutrient intake. (5.6)

6 ADVERSE REACTIONS

The most common adverse reactions are, hyperglycemia, hypersensitivity reactions, hyponatremia, infection both systemic and at the injection site, vein thrombosis or phlebitis, and electrolyte imbalance. (6)

To report SUSPECTED ADVERSE REACTIONS, contact Baxter Healthcare at 1-866-888-2472 or FDA at 1-800-FDA-1088 or www.fda.gov/medwatch.

7 DRUG INTERACTIONS

Other Products that Affect Glycemic Control, Vasopressin or Fluid and/or Electrolyte Balance: Monitor blood glucose concentrations, fluid balance, serum electrolyte concentrations and acid-base balance. (7.1)

8 USE IN SPECIFIC POPULATIONS

Pediatric Use: Increased risk of hypoglycemia/hyperglycemia; monitor serum glucose concentrations. (8.4)

FULL PRESCRIBING INFORMATION

1 INDICATIONS AND USAGE

Dextrose Injection is indicated as source of water and calories and may also be used as diluent for reconstitution of a powdered or liquid (up to 10 mL) drug product packaged in a vial with a 20 mm closure.

2 DOSAGE AND ADMINISTRATION

2.1 Important Administration Instructions

- Dextrose Injection is intended for intravenous use.
- Peripheral administration of 5% dextrose is generally acceptable, however, consider central vein when administering more than 5% dextrose or with an osmolarity of at least 900 mOsm/L or when there is peripheral vein irritation, phlebitis, and/or associated pain [see Warnings and Precautions (5.3)].
- Do not administer Dextrose Injection simultaneously with blood products through the same administration set because of the possibility of pseudoagglutination or hemolysis.
- To prevent air embolism, use a non-vented infusion set or close the vent on a vented set, avoid multiple connections, do not connect flexible containers in series, do not pressurize the flexible container to increase flow rates, and if administration is controlled by a pumping device, turn off pump before the container runs dry.
- Prior to infusion, visually inspect the diluted dextrose solution for particulate matter. The solution should be clear and there should be no precipitates. Do not administer unless solution is clear and container is undamaged.
- Use of a final filter is recommended during administration of parenteral solutions, where possible.

2.2 Recommended Dosage

The choice of dextrose concentration, rate and volume depends on the age, weight, clinical and metabolic conditions of the patient and concomitant therapy. Electrolyte supplementation may be indicated according to the clinical needs of the patient.

The administration rate should be governed, especially for premature infants with low birth weight, during the first few days of therapy, by the patient’s tolerance to dextrose.

Increase the infusion rate gradually as indicated by frequent monitoring of blood glucose concentrations [see Warnings and Precautions (5.1), Use in Specific Populations (8.4)].

2.3 Instructions for Use

To Open

- Do not remove from overpouch until ready to use.
- Tear overwrap sharply down from the slit and remove solution container. Small amounts of moisture may be found on the solution container from water permeating from inside the container. The amount of permeated water is insufficient to affect the solution significantly. If larger amounts of water are found, the container should be checked for tears or leaks.
- Visually inspect the container. Some opacity of the plastic due to moisture absorption during the sterilization process may be observed. This is normal and does not affect the solution quality or safety. The opacity will diminish gradually. Evaluate the following:
  - If the outlet port protector is damaged, detached, or not present, discard container.
  - Check to ensure the solution is clear and there are no precipitates. Discard if there is a color change and/or the appearance of precipitates, insoluble complexes or crystals.
  - Check for minute leaks by separately squeezing the inner bag firmly. If leaks are found, discard container.
  - Check that the vial adaptor cover is intact. If the vial adaptor cover is not intact, discard product.

Preparation for Administration

- Instructions for Assembly and Reconstitution: (Steps 1-3 for Assembly and steps 4-6 for Reconstitution)
  Step 1: Remove vial cover and disinfect stopper.

Step 2: Peel off foil cover. Inspect adaptor for moisture. Discard if moisture is found.

Step 3: Place vial upright and hold firmly. Push adaptor down until vial snaps in place. DO NOT TWIST. Pull vial to ensure fully seated.

Step 4: Squeeze the bag and check vial. Use only if vial is fully seated and dry. Bend adaptor tube up and down to fully break and create a visible gap in the seal.

Step 5: For liquid drug vials proceed directly to Step 6. For powdered drug vials: Hold bag with vial down. Squeeze solution into vial until half full. Shake to suspend drug in solution.

Step 6: Hold bag with vial upside down. Squeeze bag to force air into vial. Release to drain suspended drug from vial. Repeat steps 5 and 6 until vial is empty of drug and solution is thoroughly mixed. Ensure drug is completely dissolved.
Do Not Remove Drug Vial.

- Inspect the container to ensure precipitates have not formed during the mixing or addition of additives and that the solution has not changed color. Discard the admixture if either are observed.
- Insert transfer set into prepared solution container to be transferred. Follow directions accompanying transfer set.
- Remove port protector and attached administration set per its directions.
- Transfer solution by gravity. Ensure that vial is empty of drug and solution. Repeat step 6 if drug and solution remain in vial.
- Check for leaks.

To Add Medication

- Additives may be incompatible. Complete information is not available. Do not use additives known or determined to be incompatible.
- Consult with pharmacist, if available. If, in the informed judgment of the healthcare provider, it is deemed advisable to introduce additives, use aseptic technique.
- When introducing additives, consult the instructions for use of the medication to be added and other relevant literature.
- Before adding a substance or medication, verify that it is soluble and/or stable in Dextrose Injection and that the pH range of Dextrose Injection is appropriate.
  Storage
- Use promptly after admixing or dilution; do not store solutions containing additives.
- Single-dose container.
- Discard unused portion.

3 DOSAGE FORMS AND STRENGTHS

Dextrose Injection, USP is a clear, sterile, non-pyrogenic solution of 5 grams of dextrose hydrous per 100 mL (0.05 grams/mL) in 50 mL and 100 mL single-dose, flexible containers.

4 CONTRAINDICATIONS

The use of Dextrose Injection is contraindicated in patients with:

- Clinically significant hyperglycemia [see Warnings and Precautions (5.1)].
- Known hypersensitivity to dextrose [see Warnings and Precautions (5.2)].

5 WARNINGS AND PRECAUTIONS

5.1 Hyperglycemia and Hyperosmolar Hyperglycemic State

The use of dextrose infusions in patients with impaired glucose tolerance may worsen hyperglycemia. Administration of dextrose at a rate exceeding the patient’s utilization rate may lead to hyperglycemia, coma, and death.

Hyperglycemia is associated with an increase in serum osmolality, resulting in osmotic diuresis, dehydration and electrolyte losses [see Warnings and Precautions (5.5)]. Patients with underlying CNS disease and renal impairment who receive dextrose infusions, may be at greater risk of developing hyperosmolar hyperglycemic state.

Monitor blood glucose levels and treat hyperglycemia to maintain levels within normal limits while administering Dextrose Injection. Insulin may be administered or adjusted to maintain optimal blood glucose levels during Dextrose Injection administration.

5.2 Hypersensitivity Reactions

Hypersensitivity and infusion reactions including anaphylaxis, have been reported with Dextrose Injection [see Adverse Reactions (6)]. Stop infusion immediately and treat patient accordingly if signs or symptoms of a hypersensitivity reaction develop. Appropriate therapeutic countermeasures must be instituted as clinically indicated.

5.3 Vein Damage and Thrombosis

Peripheral administration of 5% Dextrose Injection is generally acceptable, however, consider central vein when administering more than 5% dextrose or with an osmolarity of ≥ 900 mOsm/L or when there is peripheral vein irritation, phlebitis, and/or associated pain [see Dosage and Administration (2.1)]. The infusion of hypertonic solutions into a peripheral vein may result in vein irritation, vein damage, and/or thrombosis. The primary complication of peripheral access is venous thrombophlebitis, which manifests as pain, erythema, tenderness or a palpable cord. Remove the catheter as soon as possible, if thrombophlebitis develops.

5.4 Hyponatremia

5% Dextrose Injection is an isotonic solution [see Description, Table 1 (11)]. In the body, however, glucose containing fluids can become extremely physiologically hypotonic due to rapid glucose metabolization. Monitoring of serum sodium is particularly important for hypotonic fluids.

Depending on the tonicity of the solution, the volume and rate of infusion, and depending on a patient’s underlying clinical condition and capability to metabolize glucose, intravenous administration of glucose can cause electrolyte disturbances, most importantly hypo- or hyperosmotic hyponatremia. Monitor serum sodium to minimize the risk of hyponatremia.

The risk for hyponatremia is increased in pediatric patients, elderly patients, postoperative patients, those with psychogenic polydipsia, and in patients treated with medications that increase the risk of hyponatremia (such as diuretics, certain antiepileptic and psychotropic medications). Close clinical monitoring may be warranted.

Acute hyponatremia can lead to acute hyponatremic encephalopathy characterized by headache, nausea, seizures, lethargy and vomiting. Patients with brain edema are at particular risk of severe, irreversible and life-threatening brain injury. Patients at increased risk for developing complications of hyponatremia, such as hyponatremic encephalopathy include pediatric patients; women, in particular, premenopausal women; patients with hypoxemia; and in patients with underlying central nervous system disease [see Use in Specific Populations (8.4, 8.5)].

Avoid Dextrose Injection in patients with or at risk for hyponatremia. If use cannot be avoided, monitor serum sodium concentrations.

Rapid correction of hyponatremia is potentially dangerous with risk of serious neurologic complications. Brain adaptations reducing risk of cerebral edema make the brain vulnerable to injury when chronic hyponatremia is too rapidly corrected, which is known as osmotic demyelination syndrome (ODS). To avoid complications, monitor serum sodium and chloride concentrations, fluid status, acid-base balance, and signs of neurologic complications.

High volume infusion must be used with close monitoring in patients with cardiac or pulmonary failure, and in patients with non-osmotic vasopressin release (including SIADH), due to the risk of hospital-acquired hyponatremia

5.5 Electrolyte Imbalance and Fluid Overload

Electrolyte deficits, particularly in serum potassium and phosphate, may occur during prolonged use of concentrated dextrose solutions.

Depending on the volume and rate of infusion, the intravenous administration of dextrose solutions can cause fluid and/or solute overloading resulting in dilution of serum electrolyte concentrations (including hypoosmotic hyponatremia, overhydration, congested states or pulmonary edema. The risk of dilutional states is inversely proportional to the electrolyte concentrations in the administered solution. The risk of solute overload causing congested states with peripheral and pulmonary edema is directly proportional to the electrolyte concentrations in the solution.

Avoid Dextrose Injection in patients with or at risk for fluid and/or solute overloading. If use cannot be avoided, monitor fluid balance, blood electrolyte levels, concentration of glucose, acid-base balance, correct fluid and electrolyte imbalances during prolonged parenteral therapy or whenever the condition of the patient or the rate of administration warrants such evaluation. Additional monitoring is recommended for patients with water and electrolyte disturbances that could be aggravated by increased glucose, insulin administration and/or free water load.

Patients at increased risk for developing hyponatremic encephalopathy include pediatric patients; elderly patients, women, in particular premenopausal women; patients with hypoxemia; and patients with underlying CNS disease [see Use in Specific Populations (8.4, 8.5)].

5.6 Refeeding Syndrome

Refeeding severely undernourished patients may result in refeeding syndrome, characterized by the intracellular shift of potassium, phosphorus, and magnesium as the patient becomes anabolic. Thiamine deficiency and fluid retention may also develop. To prevent these complications, monitor severely undernourished patients and slowly increase nutrient intakes.

6 ADVERSE REACTIONS

The following adverse reactions associated with the use of dextrose injection were identified in clinical trials or post-marketing reports. Because these reactions were reported voluntarily from a population of uncertain size, it is not always possible to estimate their frequency, reliably, or to establish a causal relationship to drug exposure.

The following clinically significant adverse reactions are described elsewhere in the labeling:

- Hyperglycemia and hyperosmolar hyperglycemic state [see Warnings and Precautions (5.1)]
- Hypersensitivity reactions: anaphylaxis, pruritis, bronchospasm, cyanosis, angioedema, hypotension, pyrexia, chills, and rash [see Warnings and Precautions (5.2)]
- Infusion Site Reactions: infusion site phlebitis, infusion site erythema, vein damage and thrombosis [see Warnings and Precautions (5.3)]
- Hyponatremia and hyponatremic encephalopathy [see Warnings and Precautions (5.4)]
- Refeeding syndrome [see Warnings and Precautions (5.6)]
- Electrolyte imbalance, fluid overload and hypervolemia [see Warnings and Precautions (5.5)]

7 DRUG INTERACTIONS

7.1 Other Products that Affect Glycemic Control or Fluid and/or Electrolyte Balance

Dextrose Injection can affect glycemic control, vasopressin and fluid and/or electrolyte balance [see Warnings and Precautions (5.1, 5.4, 5.5)]. Monitor blood glucose concentrations, fluid balance, serum electrolyte concentrations and acid-base balance when using Dextrose Injection in patients treated with other substances that affect glycemic control, vasopressin or fluid and/or electrolyte balance.

8 USE IN SPECIFIC POPULATIONS

8.1 Pregnancy

Risk Summary

Appropriate administration of Dextrose Injection during pregnancy is not expected to cause adverse developmental outcomes, including congenital malformations. Animal reproduction studies have not been conducted with injectable dextrose solutions.

The estimated background risk of major birth defects and miscarriage for the indicated population is unknown. All pregnancies have a background risk of birth defect, loss, or other adverse outcomes. In the U.S. general population, the estimated background risk of major birth defects and miscarriage in clinically recognized pregnancies is 2 to 4% and 15 to 20%, respectively.

8.2 Lactation

Risk Summary

There are no data on the presence of dextrose in human milk, the effects on a breastfed infant, or the effects on milk production. The lack of clinical data during lactation precludes a clear determination of the risk of Dextrose Injection to an infant during lactation; therefore, the developmental and health benefits of breastfeeding should be considered along with the mother’s clinical need for Dextrose Injection and any potential adverse effects on the breastfed infant from Dextrose Injection or from the underlying maternal condition.

8.4 Pediatric Use

The safety profile of Dextrose Injection in pediatric patients is similar to adults.

Neonates, especially premature infants with low birth weight, are at increased risk of developing hypo- or hyperglycemia and therefore need close monitoring during treatment with intravenous glucose infusions to ensure adequate glycemic control in order to avoid potential long-term adverse effects.

Closely monitor plasma electrolyte concentrations in pediatric patients who may have impaired ability to regulate fluids and electrolytes. In very low birth weight infants, excessive or rapid administration of Dextrose Injection may result in increased serum osmolality and risk of intracerebral hemorrhage.

Children (including neonates and older children) are at increased risk of developing hyponatremia as well as for developing hyponatremic encephalopathy [see Warnings and Precautions (5.4)].

8.5 Geriatric Use

Clinical studies of Dextrose Injection did not include sufficient numbers of subjects aged 65 and over to determine whether they respond differently from younger subjects. Elderly patients are at increased risk of developing hyponatremia as well as for developing hyponatremic encephalopathy [see Warnings and Precautions (5.4)]. Other reported clinical experience has not identified differences in responses between the elderly and younger patients. In general, dose selection for an elderly patient should be cautious, usually starting at the low end of the dosing range, reflecting the greater frequency of decreased hepatic, renal, or cardiac function, and of concomitant disease or other drug therapy.

Dextrose is known to be substantially excreted by the kidney, and the risk of toxic reactions to this drug may be greater in patients with impaired renal function. Because elderly patients are more likely to have decreased renal function, care should be taken in dose selection, and it may be useful to monitor renal function.

10 OVERDOSAGE

An increased infusion rate of Dextrose Injection or administration of dextrose solutions can cause hyperglycemia, hyperosmolality, and adverse effects on water and electrolyte balance [see Warnings and Precautions (5.1, 5.5)].

Severe hyperglycemia and severe dilutional hyponatremia, and their complications, can be fatal. Discontinue infusion, reduce dose and institute appropriate corrective measures such as administration of exogenous insulin.

Discontinue infusion and institute appropriate corrective measures in the event of overhydration or solute overload during therapy, with particular attention to CNS, respiratory and cardiovascular systems.

If over-exposure occurs, call your Poison Control Center at 1-800-222-1222 for current information on the management of poisoning or overdosage.

11 DESCRIPTION

Dextrose Injection, 5% USP is a clear, sterile, non-pyrogenic solution of Dextrose, USP in Water for Injection in a polyvinylchloride flexible plastic container for intravenous administration after admixture with a single dose powdered or liquid (up to 10 mL) drug vial [see Dosage and Administration (2.1)].

Flexible containers, designed to facilitate admixture, are available in 50 mL and 100 mL sizes. See Table 1 for the content and characteristics of this solution.

The solution contains no bacteriostatic, antimicrobial agent or added buffer and is intended only for use as a single-dose injection. The pH range is 4.0 (3.2 to 6.5).

Water can permeate from inside the container into the overwrap but not in amounts sufficient to affect the solution significantly.

Table 1. Contents and Characteristics of Dextrose Injection 5%, USP
Strength | Fill Volume | Amount of Dextrose Hydrous per Container | kcal [Caloric value calculated on the basis of 3.4 kcal/g of dextrose, hydrous] per Container | mOsmol per liter
Dextrose Injection 5%, USP (0.05 grams/mL) | 100 mL Single Pack | 5 grams | 17 | 252
Dextrose Injection 5%, USP (0.05 grams/mL) | 50 mL Single Pack | 2.5 grams | 8.5 | 252

Dextrose, USP is chemically designated D-glucose, monohydrate (C6H12O6 • H2O), a hexose sugar freely soluble in water. The molecular weight of dextrose (D-glucose) monohydrate is 198.17. It has the following structural formula:

Water for Injection, USP is chemically designated H2O.

Dextrose is derived from corn.

The Mini-Bag Plus Container System is a standard diluent container with an integral drug vial adaptor. It allows for drug admixture after connection to a single dose powdered or liquid (up to 10 mL) drug vial having a 13mm or 20mm closure. A breakaway seal in the tube between the vial adaptor and the container is broken to allow transfer of the diluent into the vial and reconstitution of a powdered or a liquid (up to 10mL) drug. The Mini-Bag Plus product mechanically prohibits the transfer of contaminants into and out of the system during and after docking, minimizing environmental and personal exposure. The reconstituted drug is then transferred from the vial into the container diluent and mixed to result in an infusion solution for delivery to the patient.

The VIAFLEX Plastic Container is fabricated from a specially formulated polyvinyl chloride (PL 146 Plastic). The amount of water that can permeate from inside the container into the overwrap is insufficient to affect the solution significantly. Solutions in contact with the plastic container can leach out certain of its chemical components in very small amounts within the expiration period, e.g., di-2-ethylhexyl phthalate (DEHP), up to 5 parts per million. However, the safety of the plastic has been confirmed in tests in animals according to USP biological tests for plastic containers as well as by tissue culture toxicity studies.

12 CLINICAL PHARMACOLOGY

12.1 Mechanism of Action

Dextrose oxidized to carbon dioxide and water, yielding energy.

16 HOW SUPPLIED/STORAGE AND HANDLING

Dextrose Injection 5%, USP is a clear, sterile solution of dextrose supplied in single-dose, flexible containers.

Product Description | Code | Size | NDC
Dextrose Injection 5%, USP (0.05 grams/mL) | EZPB0040G | 50 mL | 0338-9664-40
Dextrose Injection 5%, USP (0.05 grams/mL) | EZPB0041G | 100 mL | 0338-9666-35

Do not remove container from the overwrap until intended for use.

Use the product immediately after mixing and the introduction of additives.

Exposure of pharmaceutical products to heat should be minimized. Avoid excessive heat. It is recommended the product be stored at room temperature (25°C/77°F).

17 PATIENT COUNSELING INFORMATION

Inform patients, caregivers, or home healthcare providers of the following risks of Dextrose Injection:

- Hyperglycemia and hyperosmolar hyperglycemic state [see Warnings and Precautions (5.1)].
- Hypersensitivity reactions [see Warnings and Precautions (5.2)].
- Vein damage and thrombosis [see Warnings and Precautions (5.3)].
- Hyponatremia [see Warnings and Precautions (5.4)]
- Electrolyte imbalance and fluid overload [see Warnings and Precautions (5.5)].
- Refeeding syndrome [see Warnings and Precautions (5.6)].

Manufactured by, Packed by, Distributed by:

Baxter Healthcare Corporation
Deerfield, IL 60015 USA
Printed in Ireland

CB-30-03-106

Baxter, Mini-Bag Plus, and Viaflex are trademarks of Baxter International Inc.

PACKAGE/LABEL PRINCIPAL DISPLAY PANEL

Container Label

BREAK SEAL AND MIX BEFORE USE

EZPB0040G
NDC 0338-9664-40

50 mL

5% Dextrose
Injection USP
MINI-BAG PLUS Single Dose Container

Each 50 mL contains 2.5 g Dextrose
Hydrous USP Sterile See prescribing
information Additive compatibility
consult pharmacist For intravenous use
Do not administer simultaneously with blood
Store at Room Temperature (25°C)
Avoid Excessive Heat Rx Only

Baxter Logo
Baxter Healthcare Corporation
Deerfield IL 60015 USA
Made in Ireland

CB-35-05-582

Lot
Exp

Bar Code
(01)00303389664406

Container Label

BREAK SEAL AND MIX BEFORE USE

EZPB0041G
NDC 0338-9666-35

100 mL

5% Dextrose
Injection USP
MINI-BAG PLUS Single Dose Container

Each 100 mL contains 5 g Dextrose
Hydrous USP Sterile See prescribing
information Additive compatibility consult
pharmacist For intravenous use
Do not administer simultaneously with blood
Store at Room Temperature (25°C)
Avoid Excessive Heat Rx Only

Baxter Logo
Baxter Healthcare Corporation
Deerfield IL 60015 USA
Made in Ireland

CB-35-05-581

Lot
Exp

Bar Code
(01)00303389666356

Carton Label

Code EZPB0040G
QTY 40 x 50 mL

5% Dextrose Injection, USP
in Mini-Bag Plus Container

NDC: 0338-9664-40

Store at room temperature (25°C/77°F)
[See USP controlled room temperature]

Baxter Healthcare Corporation
Deerfield, IL 60015 USA
Made in Ireland

LOT: 88G88G88B8
EXP: YYYY/MM

Barcode
(01)50303389664401

Barcode
(01)50303389664401(17)201200(10)88G88G88B8

Code EZPB0040G
QTY 40 x 50 mL

5% Dextrose Injection, USP
in Mini-Bag Plus Container

88-46-14-247

LOT:
88G88G88B8

EXP:
YYYY/MM

Carton Label

Code EZPB0041G
QTY 35 x 100 mL

5% Dextrose Injection, USP
in Mini-Bag Plus Container

NDC: 0338-9666-35

Store at room temperature (25°C/77°F)
[See USP controlled room temperature]

Baxter Healthcare Corporation
Deerfield, IL 60015 USA
Made in Ireland

LOT: 88G88G88B8
EXP: YYYY/MM

Barcode
(01)50303389666351

Barcode
(01)50303389666351(17)201200(10)88G88G88B8

Code EZPB0041G
QTY 35 x 100 mL

5% Dextrose Injection, USP
in Mini-Bag Plus Container

88-46-14-248

LOT:
88G88G88B8

EXP:
YYYY/MM